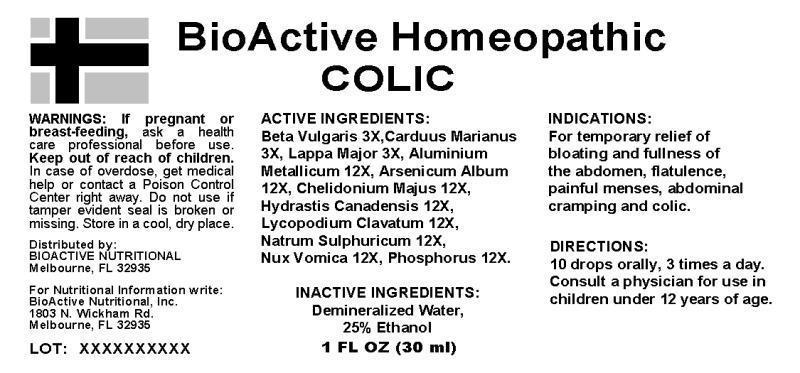 DRUG LABEL: Colic
NDC: 43857-0369 | Form: LIQUID
Manufacturer: BioActive Nutritional, Inc.
Category: homeopathic | Type: HUMAN OTC DRUG LABEL
Date: 20241017

ACTIVE INGREDIENTS: BETA VULGARIS WHOLE 3 [hp_X]/1 mL; MILK THISTLE 3 [hp_X]/1 mL; ARCTIUM LAPPA ROOT 3 [hp_X]/1 mL; ALUMINUM 12 [hp_X]/1 mL; ARSENIC TRIOXIDE 12 [hp_X]/1 mL; CHELIDONIUM MAJUS WHOLE 12 [hp_X]/1 mL; GOLDENSEAL 12 [hp_X]/1 mL; LYCOPODIUM CLAVATUM SPORE 12 [hp_X]/1 mL; SODIUM SULFATE 12 [hp_X]/1 mL; STRYCHNOS NUX-VOMICA SEED 12 [hp_X]/1 mL; PHOSPHORUS 12 [hp_X]/1 mL
INACTIVE INGREDIENTS: WATER; ALCOHOL

DRUG FACTS:

ACTIVE INGREDIENTS:

Beta Vulgaris 3X, Carduus Marianus 3X, Lappa Major 3X, Aluminium Metallicum 12X, Arsenicum Album 12X, Chelidonium Majus 12X, Hydrastis Canadensis 12X, Lycopodium Clavatum 12X, Natrum Sulphuricum 12X, Nux Vomica 12X, Phsophorus 12X.

INDICATIONS:

For temporary relief of bloating and fullness of the abdomen, flatulence, painful menses, abdominal cramping and colic.

WARNINGS:

If pregnant or breast-feeding, ask a health care professional before use.

Keep out of reach of children. In case of overdose, get medical help or contact a Poison Control Center right away.

Do not use if tamper evident seal is broken or missing.

Store in cool, dry place.

Keep out of reach of children. In case of overdose, get medical help or contact a Poison Control Center right away.

DIRECTIONS:

10 drops orally, 3 times a day. Consult a physician for use in children under 12 years of age.

INDICATIONS:

For temporary relief of bloating and fullness of the abdomen, flatulence, painful menses, abdominal cramping and colic.

INACTIVE INGREDIENTS:

Demineralized Water, 25% Ethanol

QUESTIONS:

Distributed by:

BIOACTIVE NUTRITIONAL

Melbourne, FL 32935

For Nutritional Information write:

BioActive Nutritional, Inc.

1803 N. Wickham Rd.

Melbourne, FL 32935

PACKAGE LABEL DISPLAY:

BioActive Homeopathic

COLIC

1 FL OZ (30 ml)